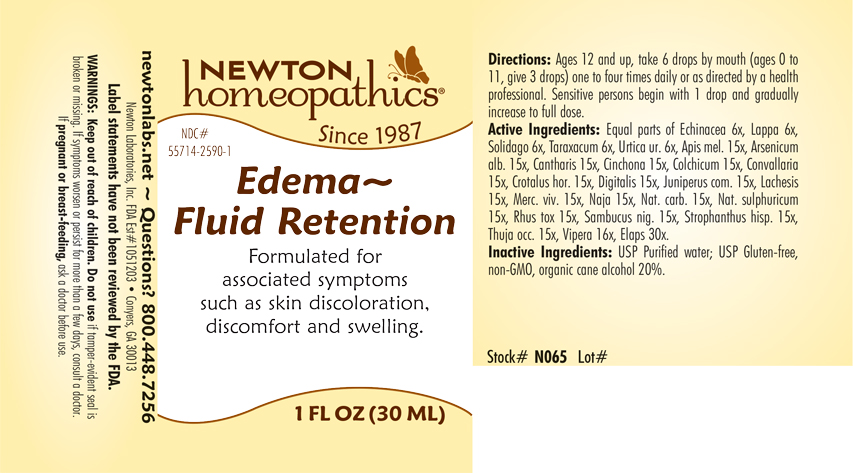 DRUG LABEL: Edema - Fluid Retention
NDC: 55714-2590 | Form: LIQUID
Manufacturer: Newton Laboratories, Inc.
Category: homeopathic | Type: HUMAN OTC DRUG LABEL
Date: 20240319

ACTIVE INGREDIENTS: MICRURUS CORALLINUS VENOM 30 [hp_X]/1 mL; APIS MELLIFERA 15 [hp_X]/1 mL; ARSENIC TRIOXIDE 15 [hp_X]/1 mL; LYTTA VESICATORIA 15 [hp_X]/1 mL; CINCHONA OFFICINALIS BARK 15 [hp_X]/1 mL; COLCHICUM AUTUMNALE BULB 15 [hp_X]/1 mL; CONVALLARIA MAJALIS 15 [hp_X]/1 mL; CROTALUS HORRIDUS HORRIDUS VENOM 15 [hp_X]/1 mL; DIGITALIS 15 [hp_X]/1 mL; LACHESIS MUTA VENOM 15 [hp_X]/1 mL; MERCURY 15 [hp_X]/1 mL; NAJA NAJA VENOM 15 [hp_X]/1 mL; SODIUM CARBONATE 15 [hp_X]/1 mL; SODIUM SULFATE 15 [hp_X]/1 mL; TOXICODENDRON PUBESCENS LEAF 15 [hp_X]/1 mL; SAMBUCUS NIGRA FLOWERING TOP 15 [hp_X]/1 mL; STROPHANTHUS HISPIDUS SEED 15 [hp_X]/1 mL; THUJA OCCIDENTALIS LEAFY TWIG 15 [hp_X]/1 mL; VIPERA BERUS VENOM 16 [hp_X]/1 mL; ECHINACEA, UNSPECIFIED 6 [hp_X]/1 mL; ARCTIUM LAPPA ROOT 6 [hp_X]/1 mL; SOLIDAGO VIRGAUREA FLOWERING TOP 6 [hp_X]/1 mL; TARAXACUM OFFICINALE 6 [hp_X]/1 mL; URTICA URENS 6 [hp_X]/1 mL; JUNIPER BERRY 15 [hp_X]/1 mL
INACTIVE INGREDIENTS: ALCOHOL; WATER

Edema 2590L

INDICATIONS & USAGE SECTION

Formulated for associated symptoms such as skin discoloration, discomfort and swelling.

DOSAGE & ADMINISTRATION SECTION

Directions: Ages 12 and up, take 6 drops by mouth (ages 0 to 11, give 3 drops) one to four times daily or as directed by a health professional. Sensitive persons begin with 1 drop and gradually increase to full dose.

OTC - ACTIVE INGREDIENT SECTION

Equal parts of Echinacea 6x, Lappa 6x, Solidago 6x, Taraxacum 6x, Urtica ur. 6x, Apis mel. 15x, Arsenicum alb. 15x, Cantharis 15x, Cinchona 15x, Colchicum 15x, Convallaria 15x, Crotalus hor. 15x, Digitalis 15x, Juniperus com.15x, Lachesis 15x, Merc. viv. 15x, Naja 15x, Nat. carb. 15x, Nat.sulphuricum 15x, Rhus tox. 15x, Sambucus nig. 15x, Strophanthus hisp. 15x, Thuja occ. 15x, Vipera 16x, Elaps 30x.

OTC - PURPOSE SECTION

Formulated for associated symptoms such as skin discoloration, discomfort and swelling.

INACTIVE INGREDIENT SECTION

Inactive Ingredients: USP Purified Water; USP Gluten-free, non-GMO, organic cane alcohol 20%.

QUESTIONS SECTION

newtonlabs.net - Questions? 800.448.7256

Newton Laboratories, Inc. FDA Est # 1051203 - Conyers, GA 30013

WARNINGS SECTION

WARNINGS: Keep out of reach of children. Do not use if tamper-evident seal is broken or missing. If symptoms worsen or persist for more than a few days, consult a doctor. If pregnant or breast-feeding, ask a doctor before use.

OTC - PREGNANCY OR BREAST FEEDING SECTION

If pregnant or breast-feeding, ask a doctor before use.

OTC - KEEP OUT OF REACH OF CHILDREN SECTION

Keep out of reach of children.